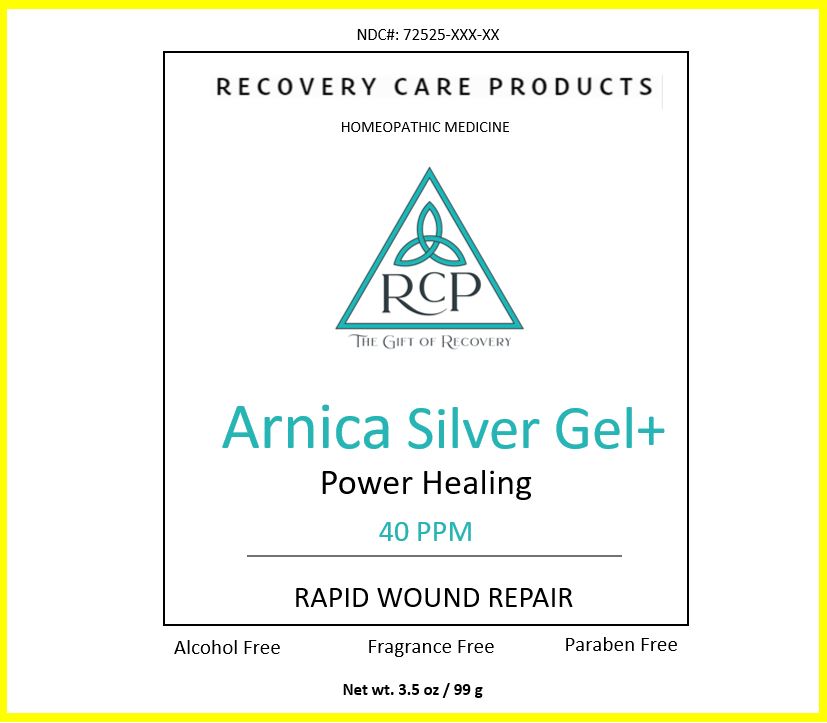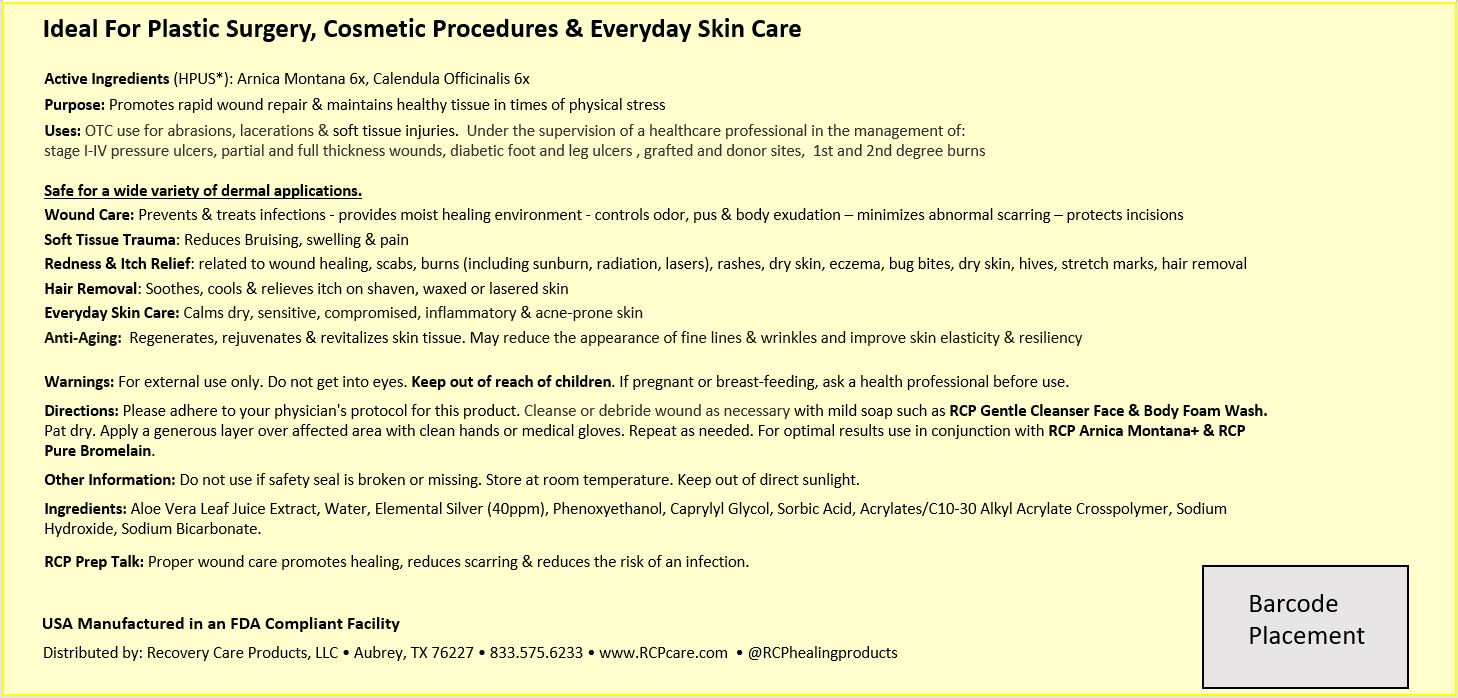 DRUG LABEL: ARNICA SILVER

NDC: 72525-005 | Form: GEL
Manufacturer: Recovery Care Products LLC
Category: homeopathic | Type: HUMAN OTC DRUG LABEL
Date: 20220117

ACTIVE INGREDIENTS: ARNICA MONTANA 6 [hp_X]/100 g; CALENDULA OFFICINALIS FLOWERING TOP 6 [hp_X]/100 g
INACTIVE INGREDIENTS: ALOE VERA LEAF; WATER; SILVER; PHENOXYETHANOL; CAPRYLYL GLYCOL; SORBIC ACID; CARBOMER INTERPOLYMER TYPE A (ALLYL SUCROSE CROSSLINKED); SODIUM HYDROXIDE; SODIUM BICARBONATE

RECOVERY CARE PRODUCTS Arnica Silver Gel+ (72525-005)

Active Ingredients (HPUS*):

ARNICA MONTANA 6X

CALENDULA OFFICINALIS 6X

(*) The letter “HPUS” indicate that the components in this products are officially monographed in the Homeopathic Pharmacopoeia of the United States. These statements have not been evaluated by the Food and Drug administration.
This product is not intended to diagnose, treat, cure or prevent any disease.

PURPOSE

Promotes rapid wound repair & maintains healthy tissue in times of physical stress

Uses:

OTC use for abrasions, lacerations & soft tissue injuries. Under the supervision of a healthcare professional in the management of:
stage I-IV pressure ulcers, partial and full thickness wounds, diabetic foot and leg ulcers , grafted and donor sites, 1st and 2nd degree burns

Safe for a wide variety of dermal applications.

Wound Care: Prevents & treats infections - provides moist healing environment - controls odor, pus & body exudation – minimizes abnormal scarring – protects incisions

Soft Tissue Trauma: Reduces Bruising, swelling & pain

Redness & Itch Relief: related to wound healing, scabs, burns (including sunburn, radiation, lasers), rashes, dry skin, eczema, bug bites, dry skin, hives, stretch marks, hair removal

Hair Removal: Soothes, cools & relieves itch on shaven, waxed or lasered skin

Everyday Skin Care: Calms dry, sensitive, compromised, inflammatory & acne-prone skin

Anti-Aging: Regenerates, rejuvenates & revitalizes skin tissue. May reduce the appearance of fine lines & wrinkles and improve skin elasticity & resiliency

Warnings:

For external use only. Do not get into eyes.

• Keep out of reach of children.

Directions:

Please adhere to your physician's protocol for this product. Cleanse or debride wound as necessary with mild soap such as RCP Gentle Cleanser Face & Body Foam Wash. Pat dry. Apply a generous layer over affected area with clean hands or medical gloves. Repeat as needed. For optimal results use in conjunction with RCP Arnica Montana+ & RCP Pure Bromelain.

Other Information:

Do not use if safety seal is broken or missing. Store at room temperature. Keep out of direct sunlight.

Inactive Ingredients:

Aloe Vera Leaf Juice Extract, Water, Elemental Silver (40ppm), Phenoxyethanol, Caprylyl Glycol, Sorbic Acid, Acrylates/C10-30 Alkyl Acrylate Crosspolymer, Sodium Hydroxide, Sodium Bicarbonate.